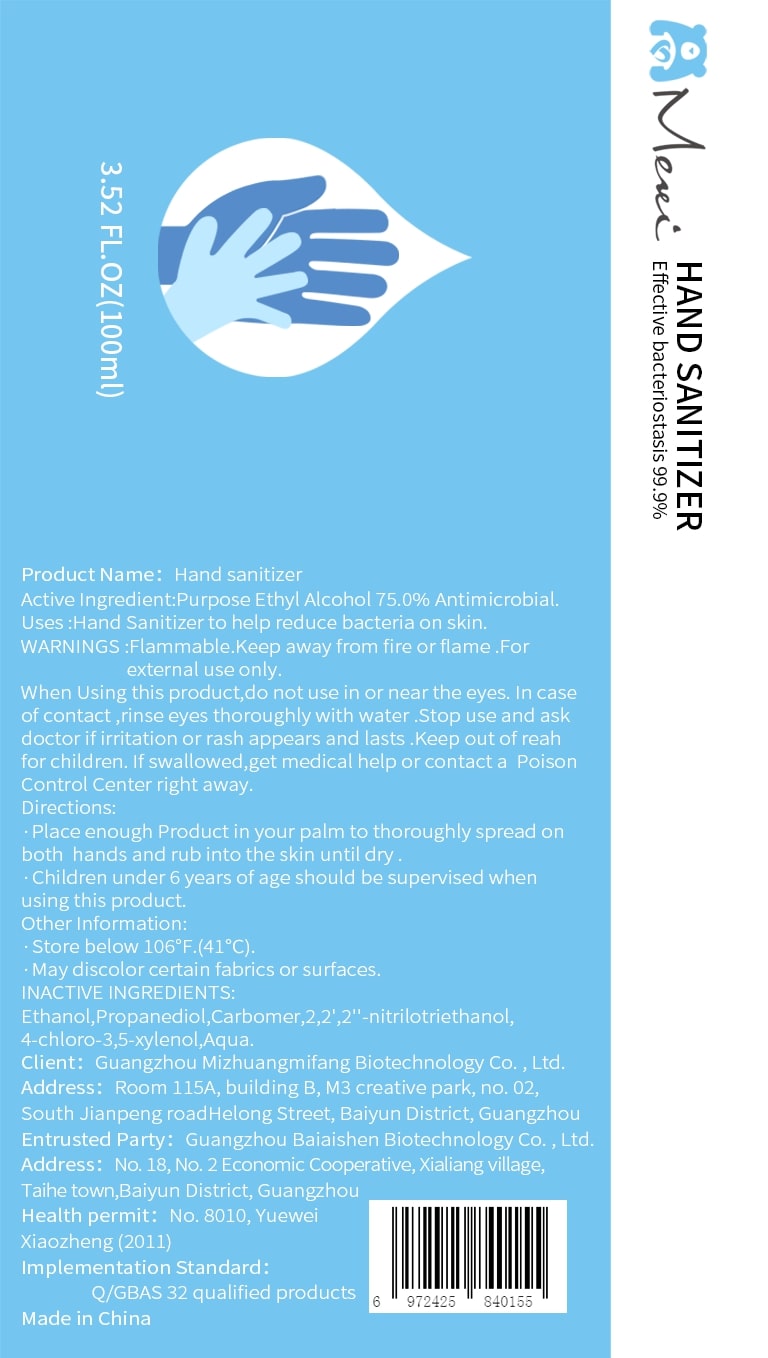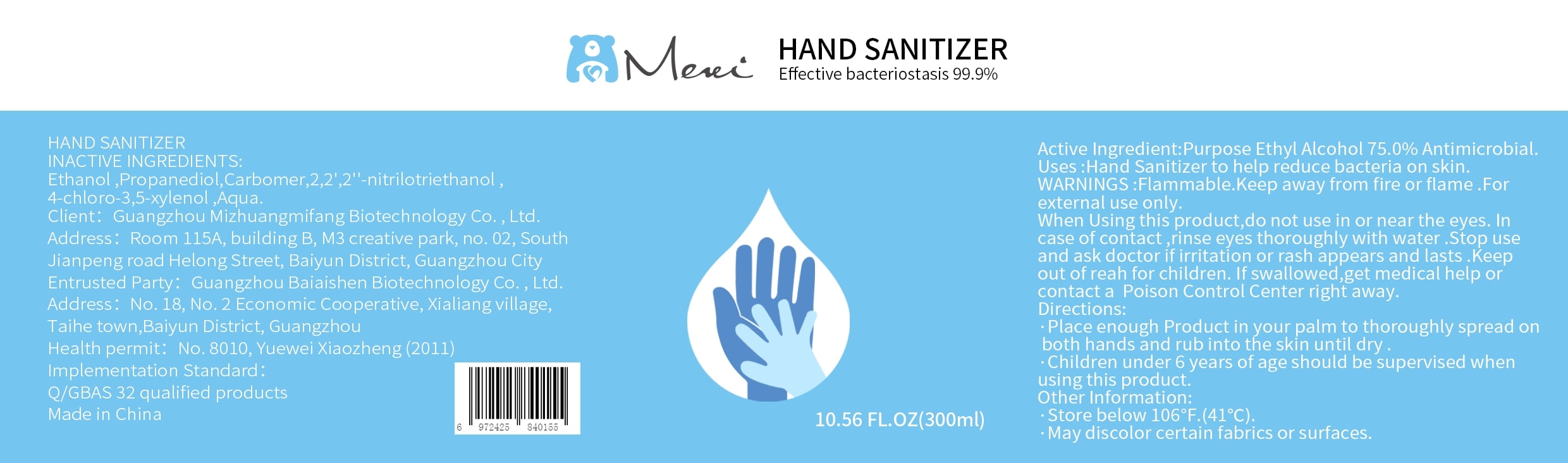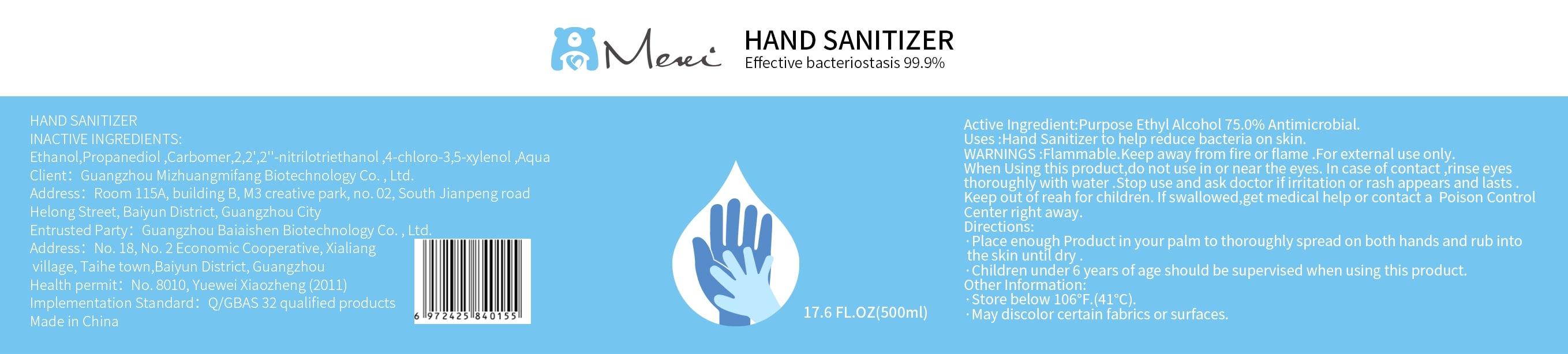 DRUG LABEL: Hand sanitizer
NDC: 74444-001 | Form: GEL
Manufacturer: Guangzhou Mizhuangmifang Biotechnology Co. , Ltd.
Category: otc | Type: HUMAN OTC DRUG LABEL
Date: 20200509

ACTIVE INGREDIENTS: ALCOHOL 75 mL/100 mL
INACTIVE INGREDIENTS: CHLOROXYLENOL; PROPANEDIOL; CARBOMER HOMOPOLYMER, UNSPECIFIED TYPE; TROLAMINE; WATER

Hand sanitizer

Active Ingredient

Ethyl Alcohol 75.0%

Purpose

Antimicrobial.

Uses

Hand Sanitizer to help reduce bacteria on skin

WARNINGS

Flammable.Keep away from fire or flame.For external use only.

When Using this product

do not use in or near the eyes.In case of contact,rinse eyes thoroughly with water.Stop use and ask doctor if irritation or rash appears and lasts.Keep out of reah for children.If swallowed,get medical help or contact a Poison Control Center right away.

Directions

Place enough Product in your palm to thoroughly spread on both hands and rub into the skin until dry.

Children under 6 years of age should be supervised when using this product.

Other Information

Store below 106°F.(41℃)

May discolor certain fabrics or surfaces.

INACTIVE INGREDIENTS

Propanediol, Carbomer,2, 2', 2”-nitrilotriethanol,4-chloro-3, 5-xylenol, Aqua.